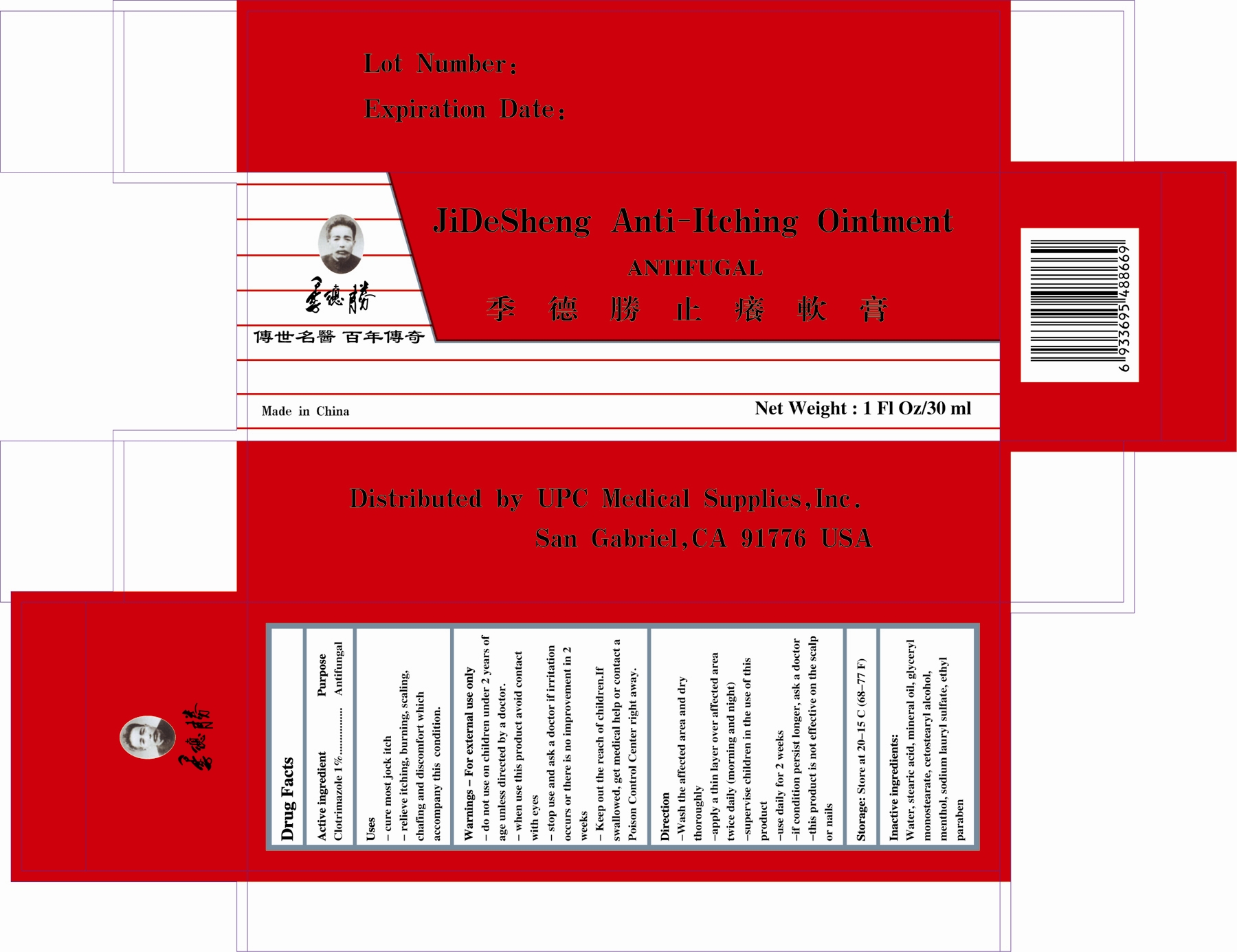 DRUG LABEL: JiDeSheng
NDC: 51849-3574 | Form: GEL
Manufacturer: Nantong Jidesheng Biology Health Care Products Co., Ltd.
Category: otc | Type: HUMAN OTC DRUG LABEL
Date: 20110331

ACTIVE INGREDIENTS: Clotrimazole 1 g/100 g
INACTIVE INGREDIENTS: Water; Mineral oil; Stearic acid; GLYCERYL MONOSTEARATE; cetostearyl alcohol; Menthol; SODIUM LAURYL SULFATE; Ethylparaben

JiDeSheng

Active ingredient Purpose
Clotrimazole 1% Antifungal

Uses
- cure most jock itch
- relieve itching, burning, scaling, chafing and discomfort which accompany this condition.

Warnings - For external use only
- do not use on children under 2 years of age unless directed by a doctor.
- when use this product avoid contact with eyes
- stop use and ask a doctor if irritation occurs or there is no improvement in 2 weeks
- Keep out the reach of children. If swallowed, get medical help or contact a Poison Control Center right away.

DOSAGE AND ADMINISTRATION

Direction
- Wash the affected area and dry thoroughly
- apply a thin layer over affected area twice daily (morning and night)
- supervise children in the use of this product
- use daily for 2 weeks
- if condition persist longer, ask a doctor
- this product is not effective on the scalp or nails

STORAGE AND HANDLING

Storage: Store at 20-15 C (68-77 F)

Inactive ingredients:
Water, stearic acid, mineral, glyceryl monostearate, cetostearyl alcohol, menthol, sodium lauryl sulfate, ethyl paraben

stop use and ask a doctor if irritation occurs or there is no improvement in 2 weeks

Keep out of reach of children. In case of overdose, get medical help or contact a Poison Control Center right away.

do not use on children under 2 years of age unless directed by a doctor.

PURPOSE

Antifungal

PACKAGE LABEL

JiDeSheng Anti-Itching Ointment
ANTIFUNGAL
Uses to relieve itching, burning, scaling, chafing and discomfort which accompany this condition.
For external use only
Product of China
Net wt. 1 oz. (30g)